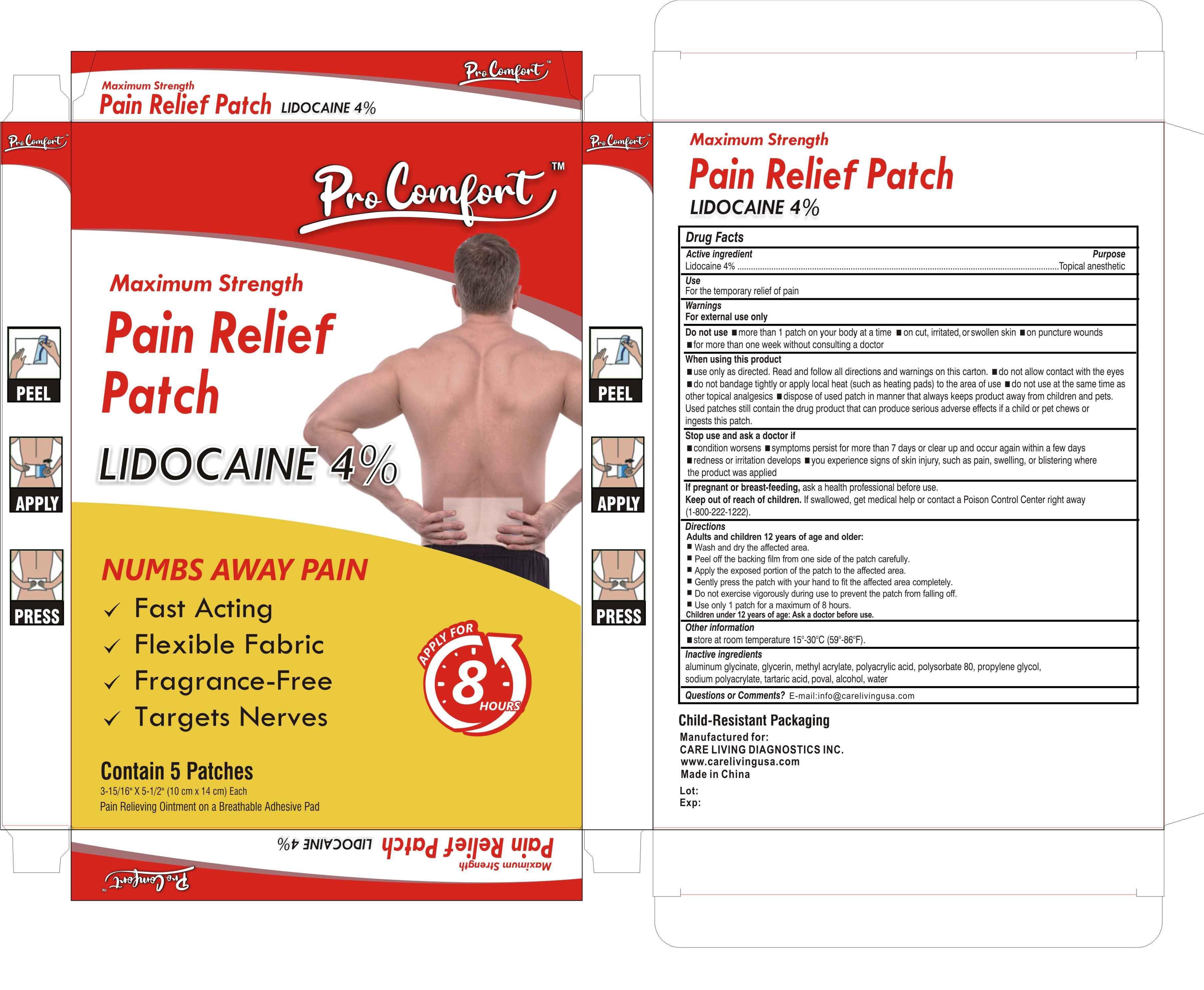 DRUG LABEL: Pro Comfort 8 Hours Patch
NDC: 83568-4643 | Form: PATCH
Manufacturer: CARE LIVING DIAGNOSTICS INC
Category: otc | Type: HUMAN OTC DRUG LABEL
Date: 20230729

ACTIVE INGREDIENTS: LIDOCAINE 4 g/100 g
INACTIVE INGREDIENTS: DIHYDROXYALUMINUM AMINOACETATE ANHYDROUS; GLYCERIN; POLYACRYLIC ACID (8000 MW); POLYSORBATE 80; PROPYLENE GLYCOL; SODIUM POLYACRYLATE (8000 MW); TARTARIC ACID; TITANIUM DIOXIDE; UREA; ALCOHOL; WATER

Product Information

Active Ingredient

Lidocaine 4% . . . . . . . . . . . . . . . . . . . . . . . . . . . . . .

Purpose

Topical Anesthetic

Uses

for the temporary relief of pain

Warnings

For external use only

Do not use

- more than 1 patch on your body at a time
- on puncture wounds,
- on cuts, irritated or swollen skin
- for more than one week without consulting a doctor

When using this product

- use only as directed. Read and follow all directions and warnings on this carton.
- do not allow contact with the eyes
- do not bandage tightly or apply local heat (such as heating pads) to the area of use
- do not use at the same time as other topical analgesics
- dispose of used patch in manner that always keeps product away from children and pets. Used patches still contain the drug product that can produce serious adverse effects if a child or pet chews or ingests this patch

Stop use and ask a doctor if

- condition worsens
- symptoms persist for more than 7 days or clear up and occur again within a few days
- redness or irritation develops
- you experience signs of skin injury, such as pain, swelling, or blistering where the product was applied

If pregnant or breast-feeding,

ask a health professional before use.

Keep out of reach of children and pets.

If swallowed, get medical help or contact a Poison Control Center right away (1-800-222-1222).

Directions

Adults and children over 12 years:

- wish and dry affected area
- Peel off the backing fim from one side of the patch carefully
- Apply the exposed portion of the patch to the affected area
- Gently press the patch with your hand to fit the affected area completely
- Do not exercise vigorously during use to prevent the patch from falling off
- use only 1 patch for a maximum of 8 hours

children under 12 years of age: Ask a doctor before use

Other Information

store at room temperature 15°-30°C (59°-86°F).

Inactive ingredients

aluminum glycinate, glycerin, methyl acrylate, polyacrylic acid, polysorbate 80, propylene glycol, sodium polyacrylate, tartaric acid, poval, alcohol, water

Questions or Comments?
E-mail: info@carelivingusa.com

Child-Resistant Packaging
Manufactured for

CARE LIVING DIAGNOSTICS INC.

Www.carelivingusa.com

Made in China

Active Ingredient

Lidocaine 4%

Purpose

Topical anesthetic

Uses

for the temporary relief of pain

Warnings

For external use only

Do not use

- more than 1 patch on your body at a time
- on puncture wounds,
- on cuts, irritated or swollen skin
- for more than one week without consulting a doctor

When using this product

- use only as directed. Read and follow all directions and warnings on this carton.
- do not allow contact with the eyes
- do not bandage tightly or apply local heat (such as heating pads) to the area of use
- do not use at the same time as other topical analgesics
- dispose of used patch in manner that always keeps product away from children and pets.
- Used patches still contain the drug product that can produce serious adverse effects if a child or pet chews or ingests this patch

Stop use and ask a doctor if

- condition worsens
- symptoms persist for more than 7 days or clear up and occur again within a few days
- redness or iritation develops
- you experience signs of skin injury, such as pain, swelling, or blistering wherethe product was applied

If pregnant or breast-feeding,

ask a health professional before use

Keep out of reach of children and pets.

lf swallowed, get medical help or contact a Poison Control Center right away(1-800-222-1222)

Directions

Adults and children 12 years of age and older:

- Wash and dry the affected area.
- Peel off the backing film from one side of the patch carefully.
- Apply the exposed portion of the patch to the affected area.
- Gently press the patch with your hand to fit the affected area completely.
- Do not exercise vigorously during use to prevent the patch from falling off.
- Ues only 1 patch for a maximum of 8 hours.

children under 12 years of age: Ask a doctor before use.

Other Information

store at room temperature 15°-30°C (59°-86°F).

Inactive ingredients

aluminum glycinate, glycerin, methyl acrylate, polyacrylic acid, polysorbate 80, propylene glycol, sodium polyacrylate, tartaric acid, poval, alcohol, water

Questions or Comments?

E-mail:info@carelivingusa.com

Manufactured for:

CARE LIVING DIAGNOSTICSINC

www.carelivingusa.com

Made in China

Dosage

0.246 g in 1 PATCH,5 PATCH in 1 CARTON